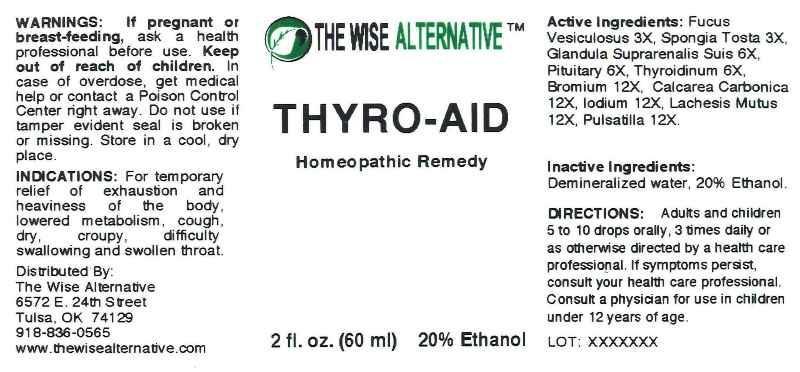 DRUG LABEL: Thyro Aid
NDC: 51096-0007 | Form: LIQUID
Manufacturer: The Wise Alternative
Category: homeopathic | Type: HUMAN OTC DRUG LABEL
Date: 20130318

ACTIVE INGREDIENTS: FUCUS VESICULOSUS 3 [hp_X]/1 mL; SPONGIA OFFICINALIS SKELETON, ROASTED 3 [hp_X]/1 mL; SUS SCROFA ADRENAL GLAND 6 [hp_X]/1 mL; SUS SCROFA PITUITARY GLAND 6 [hp_X]/1 mL; SUS SCROFA THYROID 6 [hp_X]/1 mL; BROMINE 12 [hp_X]/1 mL; OYSTER SHELL CALCIUM CARBONATE, CRUDE 12 [hp_X]/1 mL; IODINE 12 [hp_X]/1 mL; LACHESIS MUTA VENOM 12 [hp_X]/1 mL; PULSATILLA VULGARIS 12 [hp_X]/1 mL
INACTIVE INGREDIENTS: WATER; ALCOHOL

Drug Facts

ACTIVE INGREDIENTS

Fucus Vesiculosus 3X, Spongia Tosta 3X, Glandula Suprarenalis Suis 6X, Pituitary (Suis) 6X, Thyroidinum (Suis) 6X, Bromium 12X, Calcarea Carbonica 12X, Iodium 12X, Lachesis Mutus 12X, Pulsatilla 12X

INDICATIONS

For temporary relief of exhaustion and heaviness of the body, lowered metabolism, cough, dry, croupy, difficulty swallowing and swollen throat.

WARNINGS

If pregnant or breast-feeding, ask a health professional before use. Keep out of reach of children. In case of overdose, get medical help or contact a Poison Control Center right away. Do not use if tamper evident seal is broken or missing. Store in a cool, dry place.

DIRECTIONS

Adults and children 5 to 10 drops orally, 3 times daily or as otherwise directed by a health care professional. If symptoms persist, consult your health care professional. Consult a physician for use in children under 12 years of age.

INACTIVE INGREDIENTS

Demineralized water, 20% Ethanol.

KEEP OUT OF REACH OF CHILDREN

In case of overdose, get medical help or contact a Poison Control Center right away.

INDICATIONS AND USAGE

For temporary relief of exhaustion and heaviness of the body, lowered metabolism, cough, dry, croupy, difficulty swallowing and swollen throat.

QUESTIONS

Distributed By:

The Wise Alternative

6572 E. 24th Street

Tulsa, OK 74129

918-836-0565

www.thewisealternative.com

PACKAGE LABEL

THE WISE ALTERNATIVE

THYRO AID

Homeopathic Remedy

2 fl. oz. (60 ml)